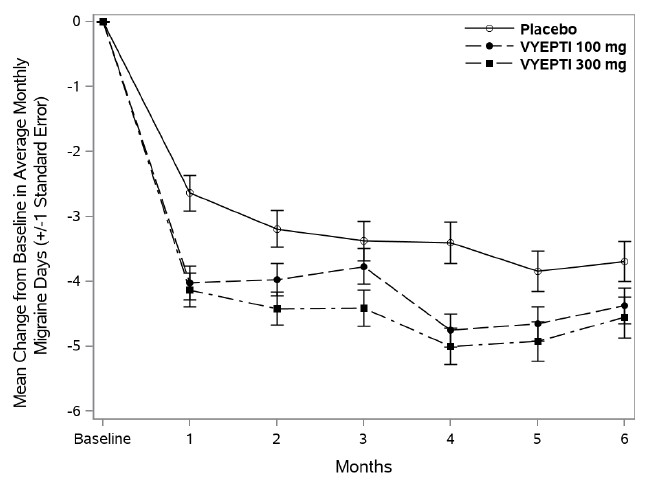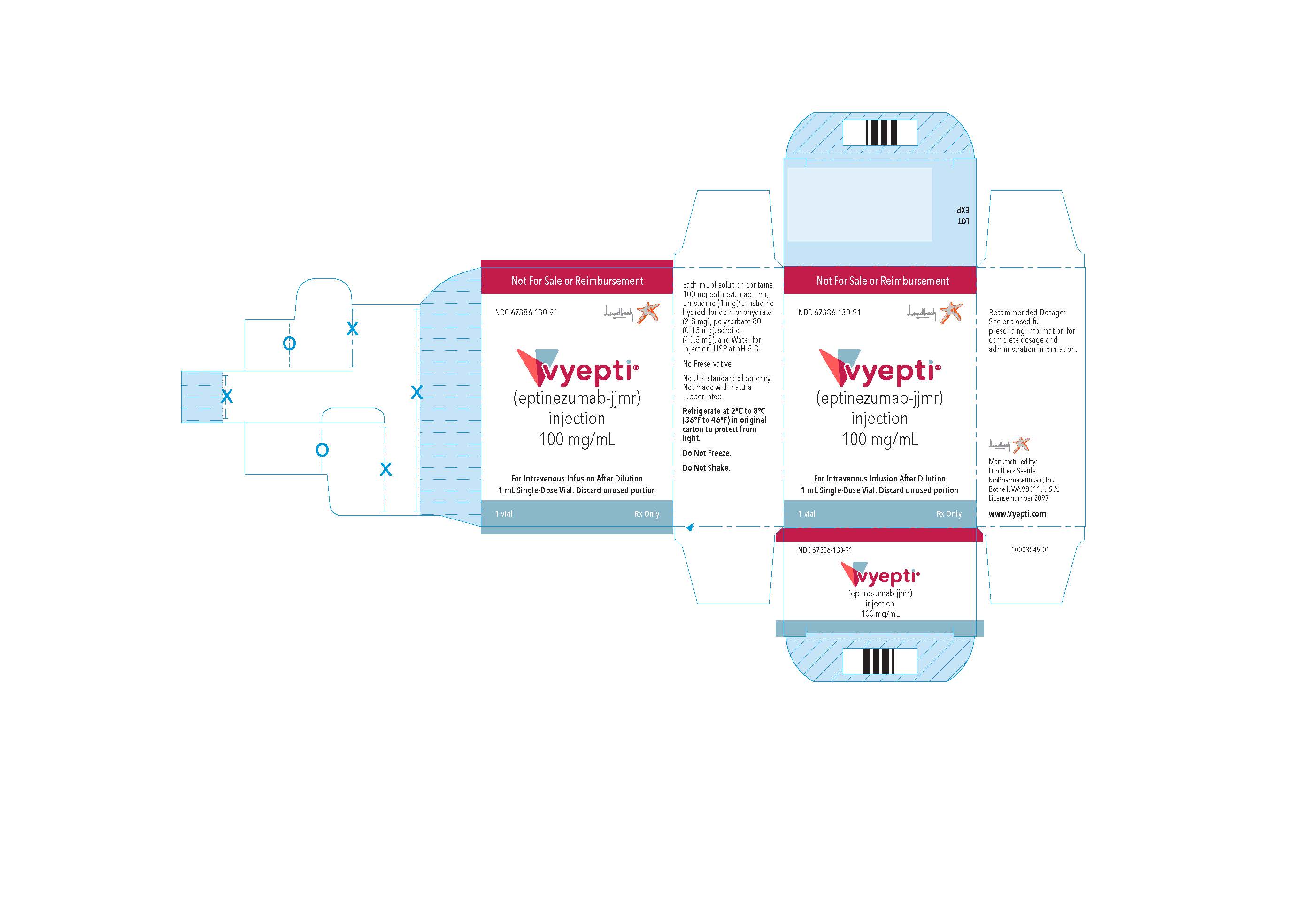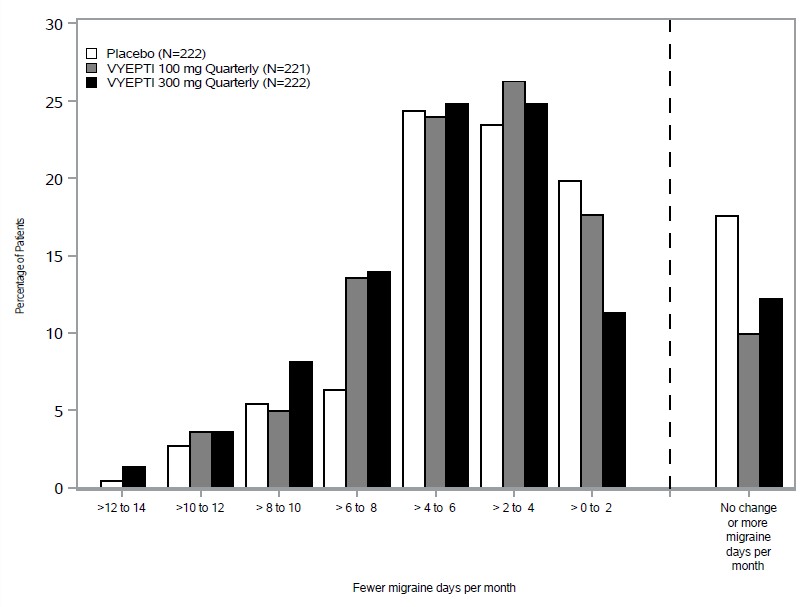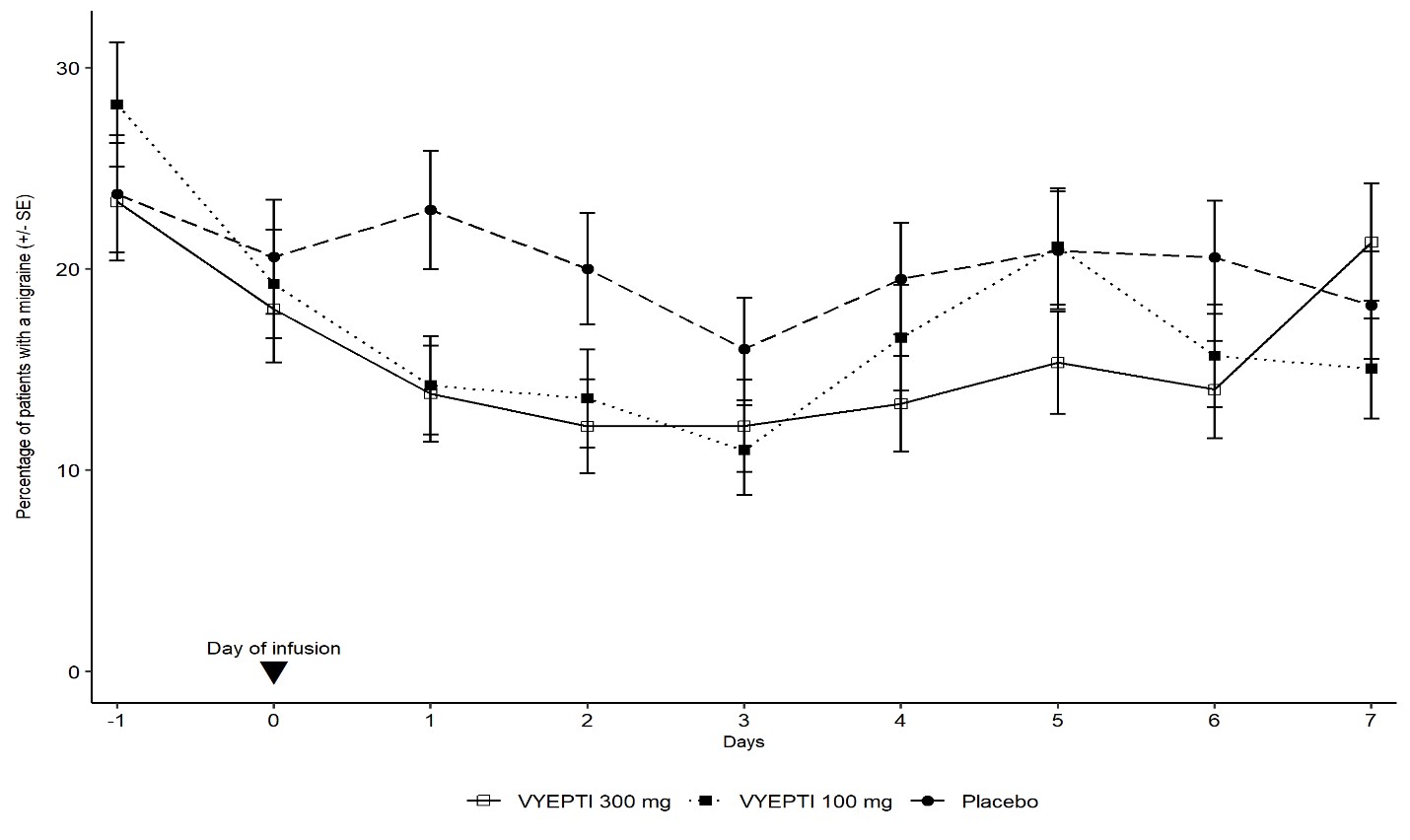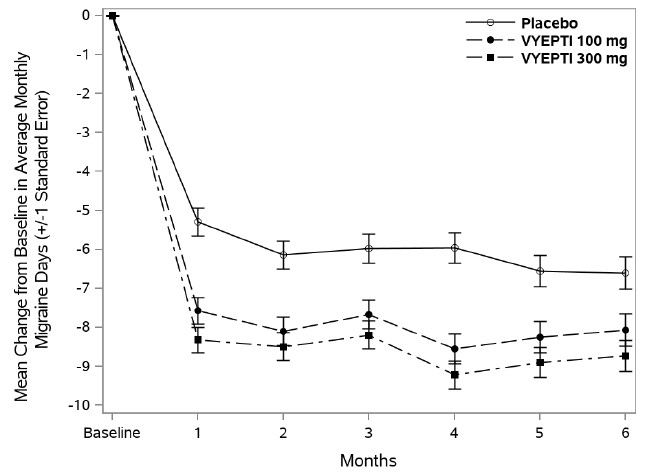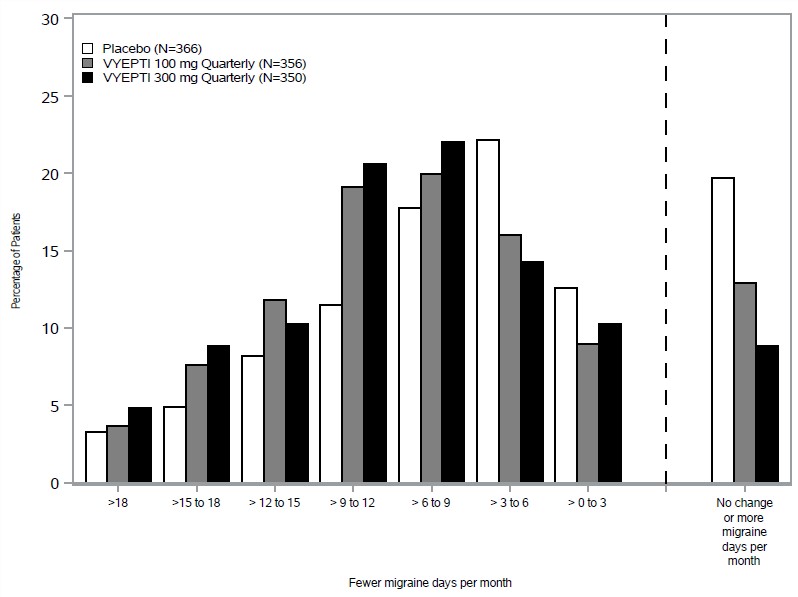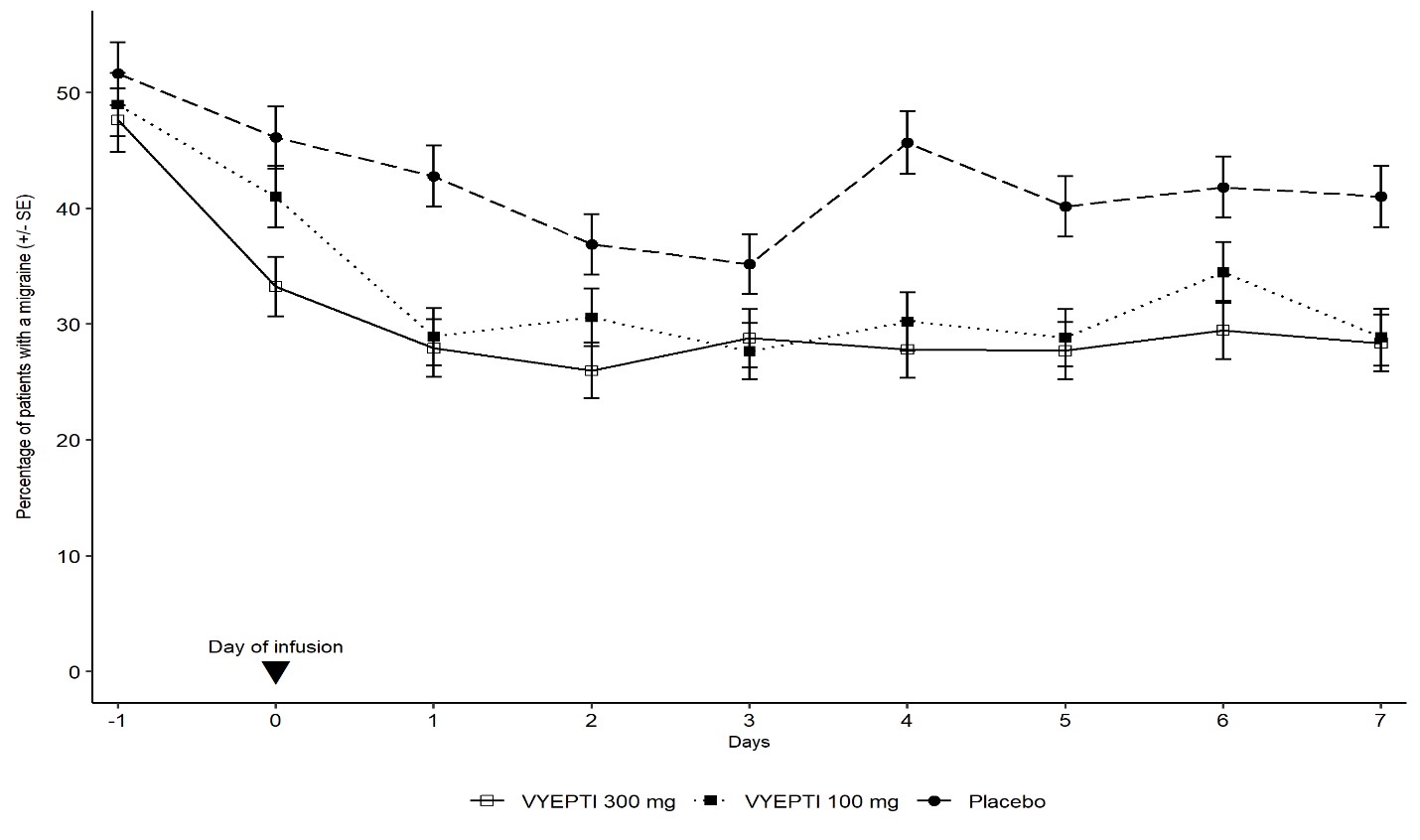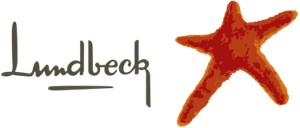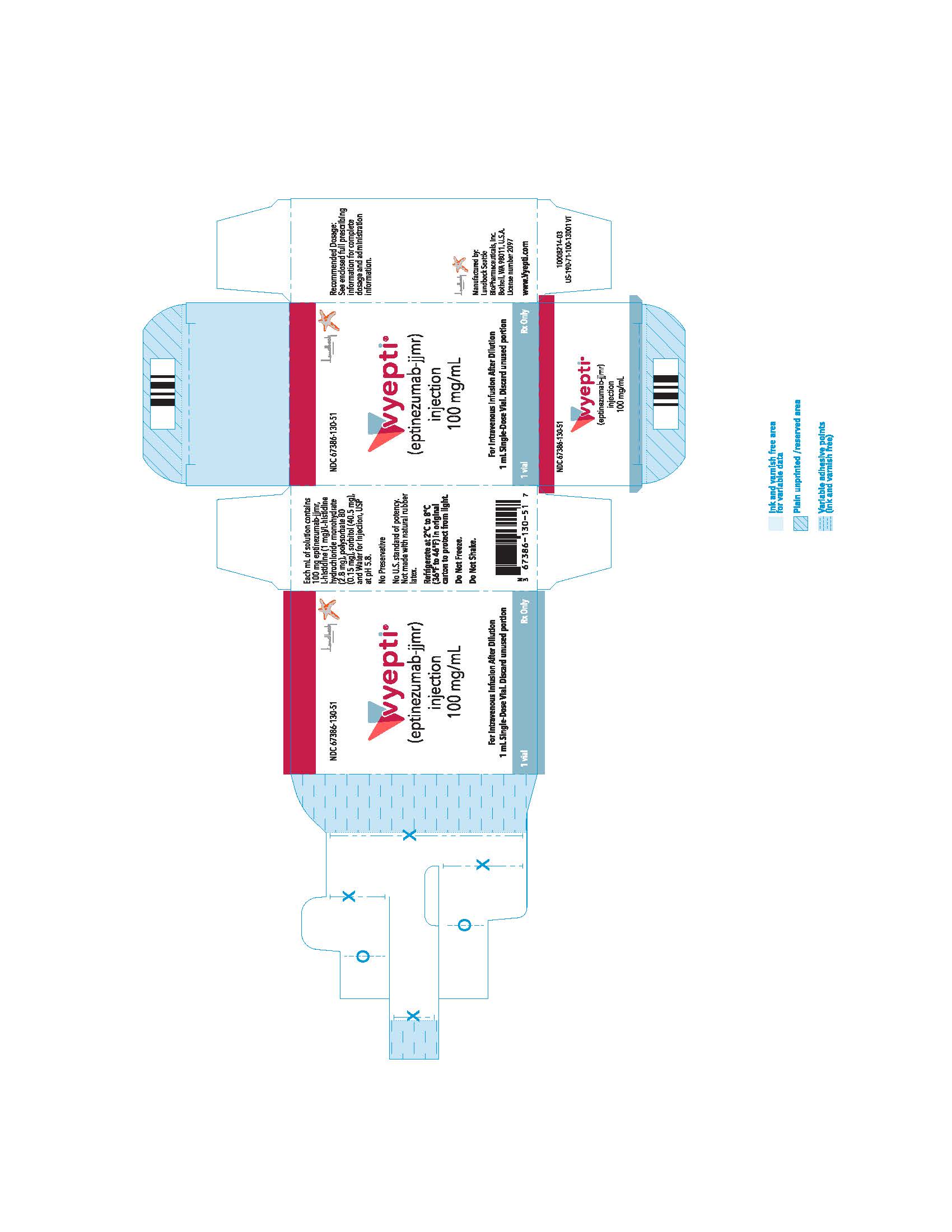 DRUG LABEL: Vyepti
NDC: 67386-130 | Form: INJECTION
Manufacturer: Lundbeck Pharmaceuticals LLC
Category: prescription | Type: HUMAN PRESCRIPTION DRUG LABEL
Date: 20251022

ACTIVE INGREDIENTS: EPTINEZUMAB 100 mg/1 mL
INACTIVE INGREDIENTS: HISTIDINE; HISTIDINE MONOHYDROCHLORIDE MONOHYDRATE; POLYSORBATE 80; SORBITOL; WATER

HIGHLIGHTS OF PRESCRIBING INFORMATION

These highlights do not include all the information needed to use VYEPTI safely and effectively. See full prescribing information for VYEPTI.
VYEPTI® (eptinezumab-jjmr) injection, for intravenous use
Initial U.S. Approval: 2020

RECENT MAJOR CHANGES

Warnings and Precautions (5.2, 5.3) 3/2025

1 INDICATIONS AND USAGE

VYEPTI is a calcitonin gene-related peptide antagonist indicated for the preventive treatment of migraine in adults (1)

2 DOSAGE AND ADMINISTRATION

- Must dilute before use. For intravenous infusion only (2.1, 2.2)
- Recommended dosage is 100 mg as an intravenous infusion over approximately 30 minutes every 3 months. Some patients may benefit from a dosage of 300 mg every 3 months (2.1, 2.3)
- Dilute only in 100 mL of 0.9% Sodium Chloride Injection (2.2)

3 DOSAGE FORMS AND STRENGTHS

Injection: 100 mg/mL solution in a single-dose vial (3)

4 CONTRAINDICATIONS

VYEPTI is contraindicated in patients with serious hypersensitivity to eptinezumab-jjmr or to any of the excipients (4)

5 WARNINGS AND PRECAUTIONS

- Hypersensitivity Reactions: If a hypersensitivity reaction occurs, consider discontinuing VYEPTI and initiate appropriate therapy (5.1)
- Hypertension: New-onset or worsening of pre-existing hypertension may occur (5.2)
- Raynaud’s Phenomenon: New-onset or worsening of pre-existing Raynaud’s phenomenon may occur (5.3)

6 ADVERSE REACTIONS

The most common adverse reactions (≥2% and 2% or greater than placebo) were nasopharyngitis and hypersensitivity (6.1)

To report SUSPECTED ADVERSE REACTIONS, contact Lundbeck at 1-800-455-1141 or FDA at 1-800-FDA-1088 or www.fda.gov/medwatch.

FULL PRESCRIBING INFORMATION

1 INDICATIONS AND USAGE

VYEPTI is indicated for the preventive treatment of migraine in adults.

2 DOSAGE AND ADMINISTRATION

2.1 Recommended Dosing

The recommended dosage is 100 mg administered by intravenous infusion every 3 months. Some patients may benefit from a dosage of 300 mg administered by intravenous infusion every 3 months.

2.2 Dilution Instructions

VYEPTI requires dilution prior to administration. Dilute only in 100 mL 0.9% Sodium Chloride Injection, USP. The infusion bags must be made of polyvinyl chloride (PVC), polyethylene (PE), or polyolefin (PO). Use appropriate aseptic technique when preparing VYEPTI solution for intravenous infusion. VYEPTI single-dose vials contain no preservative; discard unused portion remaining in the vial.

Dilution

100 mg dose:

To prepare the solution, withdraw 1 mL of VYEPTI from a single-dose vial using a sterile needle and syringe. Inject the 1 mL content into a 100 mL bag of 0.9% Sodium Chloride Injection, USP.

300 mg dose:

To prepare the solution, withdraw 1 mL of VYEPTI from each of 3 single-dose vials using a sterile needle and syringe. Inject the resulting 3 mL content into a 100 mL bag of 0.9% Sodium Chloride Injection, USP.

Storage and Handling of Diluted Product

Gently invert the VYEPTI solution to mix completely. Do not shake. Following dilution, VYEPTI solution must be infused within 8 hours. During this time, VYEPTI solution should be stored at room temperature, 20°C to 25°C (68°F to 77°F). Do not freeze.

2.3 Infusion Administration Instructions

Parenteral drug products should be inspected visually for particulate matter and discoloration prior to administration, whenever solution and container permit. Do not use if the liquid contains visible particulate matter or is cloudy or discolored [see Dosage Forms and Strengths (3)].

No other medications should be administered through the infusion set or mixed with VYEPTI. VYEPTI is for intravenous infusion only; infuse over approximately 30 minutes. Do not administer VYEPTI as an intravenous push or bolus injection. Use an intravenous infusion set with a 0.2 micron or 0.22 micron in-line or add-on sterile filter. After the infusion is complete, flush the line with 20 mL of 0.9% Sodium Chloride Injection, USP.

3 DOSAGE FORMS AND STRENGTHS

VYEPTI is a clear to slightly opalescent, colorless to brownish-yellow solution available as follows:

- Injection: 100 mg/mL in a single-dose vial

4 CONTRAINDICATIONS

VYEPTI is contraindicated in patients with serious hypersensitivity to eptinezumab-jjmr or to any of the excipients in VYEPTI. Reactions have included anaphylaxis and angioedema [see Warnings and Precautions (5.1)].

5 WARNINGS AND PRECAUTIONS

5.1 Hypersensitivity Reactions

Hypersensitivity reactions, including angioedema, urticaria, facial flushing, dyspnea, and rash, have occurred with VYEPTI in clinical trials and in the postmarketing setting. Most hypersensitivity reactions occurred during infusion and were not serious, but often led to discontinuation or required treatment. Serious hypersensitivity reactions may occur. Cases of anaphylaxis have been reported in the postmarketing setting. If a hypersensitivity reaction occurs, consider discontinuing VYEPTI and institute appropriate therapy [see Contraindications (4) and Patient Counseling Information (17)].

5.2 Hypertension

Development of hypertension and worsening of pre-existing hypertension have been reported following the use of CGRP antagonists, including VYEPTI, in the postmarketing setting. Some of the patients who developed new-onset hypertension had risk factors for hypertension. There were cases requiring initiation of pharmacological treatment for hypertension, and in some cases hospitalization. Hypertension may occur at any time during treatment, but was most frequently reported within 7 days of therapy initiation. The CGRP antagonist was discontinued in many of the reported cases.

Monitor patients treated with VYEPTI for new-onset hypertension or worsening of pre-existing hypertension, and consider whether discontinuation of VYEPTI is warranted if evaluation fails to establish an alternative etiology or blood pressure is inadequately controlled.

5.3 Raynaud’s Phenomenon

Development of Raynaud’s phenomenon and recurrence or worsening of pre-existing Raynaud’s phenomenon have been reported in the postmarketing setting following the use of CGRP antagonists. In reported cases with monoclonal antibody CGRP antagonists, symptom onset occurred a median of 71 days following dosing. Many of the cases reported serious outcomes, including hospitalizations and disability, generally related to debilitating pain. In most reported cases, discontinuation of the CGRP antagonist resulted in resolution of symptoms.

VYEPTI should be discontinued if signs or symptoms of Raynaud’s phenomenon develop, and patients should be evaluated by a healthcare provider if symptoms do not resolve. Patients with a history of Raynaud’s phenomenon should be monitored for, and informed about the possibility of, worsening or recurrence of signs and symptoms.

6 ADVERSE REACTIONS

The following clinically significant adverse reactions are described elsewhere in the labeling:

- Hypersensitivity Reactions [see Warnings and Precautions (5.1)].
- Hypertension [see Warnings and Precautions (5.2)]
- Raynaud’s Phenomenon [see Warnings and Precautions (5.3)]

6.1 Clinical Trials Experience

Because clinical trials are conducted under widely varying conditions, adverse reaction rates observed in the clinical trials of a drug cannot be directly compared to rates in the clinical trials of another drug and may not reflect the rates observed in clinical practice.

The safety of VYEPTI was evaluated in 2076 patients with migraine who received at least one dose of VYEPTI, representing 1615 patient-years of exposure; of these, 1524 patients were exposed to 100 mg or 300 mg. Across all doses, 1872 patients were exposed for at least 6 months and 991 patients were exposed for 12 months. In the placebo-controlled clinical studies (Study 1 and Study 2) of 1372 patients, 579 patients received at least one dose of VYEPTI 100 mg, 574 patients received at least one dose of VYEPTI 300 mg, and 588 patients received placebo [see Clinical Studies (14)]. Approximately 86% were female, 89% were white, and the mean age was 40.4 years at study entry.

The most common (incidence at least 2% and at least 2% greater than placebo) adverse reactions in the clinical trials for the preventive treatment of migraine were nasopharyngitis and hypersensitivity.

Table 1 summarizes the adverse reactions that occurred during Study 1 and Study 2.

Table 1. Adverse Reactions Occurring with an Incidence of at Least 2% for VYEPTI and at Least 2% Greater than Placebo in Studies 1 and 2

Adverse Reactions | VYEPTI 100 mg N=579% | VYEPTI 300 mg N=574% | Placebo N=588%
Nasopharyngitis | 6 | 8 | 6
Hypersensitivity reactions* | 1 | 2 | 0

* Hypersensitivity reactions includes multiple related adverse event terms, such as hypersensitivity, pruritus, and flushing/hot flush that occurred on the day of dosing.

In Study 1 and Study 2, 1.9% of patients treated with VYEPTI discontinued treatment because of adverse reactions [see Warnings and Precautions (5.1)].

In study 3, the safety profile observed in 480 patients who were randomized and treated (238 to VYEPTI 100 mg and 242 to placebo) was consistent with the safety profile observed in the two pivotal placebo-controlled studies with VYEPTI (Study 1 and 2).

6.2 Postmarketing Experience

The following adverse reactions have been identified during postapproval use of VYEPTI. Because these reactions are reported voluntarily from a population of uncertain size, it is not always possible to reliably estimate their frequency or establish a causal relationship to drug exposure.

Immune System Disorders: Anaphylaxis [see Contraindications (4) and Warnings and Precautions (5.1)]

General Disorders and Administration Site Conditions: Fatigue

Vascular Disorders: Hypertension [see Warnings and Precautions (5.2)], Raynaud’s phenomenon [see Warnings and Precautions (5.3)]

8 USE IN SPECIFIC POPULATIONS

8.1 Pregnancy

Pregnancy Exposure Registry

There is a pregnancy exposure registry that monitors pregnancy outcomes in women exposed to VYEPTI during pregnancy. Healthcare providers are encouraged to register pregnant patients, or pregnant women may enroll themselves in the registry by calling 1-855-810-8549 or by contacting the company at www.vyeptipregnancyregistry.lundbeck.com.

Risk Summary

There are no adequate data on developmental risks associated with the use of VYEPTI in pregnant women.

No adverse developmental effects were observed following administration of eptinezumab-jjmr to pregnant animals at doses greater than those used clinically [see Data].

In the U.S. general population, the estimated background risk of major birth defects and miscarriages in clinically recognized pregnancies is 2%-4% and 15%-20%, respectively. The estimated rate of major birth defects (2.2%-2.9%) and miscarriage (17%) among deliveries to women with migraine are similar to rates reported in women without migraine.

Clinical Considerations

Disease-Associated Maternal and/or Embryo/Fetal Risk

Published data have suggested that women with migraine may be at increased risk of preeclampsia and gestational hypertension during pregnancy.

Data

Animal Data

When eptinezumab-jjmr (0, 75, or 150 mg/kg) was administered weekly to female rats and rabbits by intravenous injection throughout organogenesis, no adverse effects on embryofetal development were observed. The higher dose tested (150 mg/kg) is 30 times the maximum recommended human dose (MRHD) of 300 mg, on a body weight basis (mg/kg).

When eptinezumab-jjmr (0, 75, or 150 mg/kg) was administered weekly to female rats throughout pregnancy and lactation, no adverse effects on pre- and postnatal development were observed. The higher dose tested (150 mg/kg) is 30 times the MRHD, on a mg/kg basis.

8.2 Lactation

Risk Summary

There are no data on the presence of eptinezumab-jjmr in human milk, the effects on the breastfed infant, or the effects on milk production. The developmental and health benefits of breastfeeding should be considered along with the mother’s clinical need for VYEPTI and any potential adverse effects on the breastfed infant from VYEPTI or from the underlying maternal condition.

8.4 Pediatric Use

Safety and effectiveness in pediatric patients have not been established.

8.5 Geriatric Use

Clinical studies of VYEPTI did not include sufficient numbers of patients aged 65 and over to determine whether they respond differently from younger patients.

11 DESCRIPTION

Eptinezumab-jjmr is a humanized immunoglobulin G1 (IgG1) monoclonal antibody specific for calcitonin gene-related peptide (CGRP) ligand. Eptinezumab-jjmr has an approximate molecular weight of 143 kD. Eptinezumab-jjmr is produced in Pichia pastoris yeast cells by recombinant DNA technology.

VYEPTI (eptinezumab-jjmr) injection is a sterile, preservative-free, clear to slightly opalescent, colorless to brownish-yellow solution, for intravenous infusion. VYEPTI is supplied as a 100 mg/mL single-dose vial. Each mL contains 100 mg eptinezumab-jjmr formulated in L-histidine (1 mg), L-histidine hydrochloride monohydrate (2.8 mg), polysorbate 80 (0.15 mg), sorbitol (40.5 mg), and Water for Injection, USP, at a pH of 5.8.

12 CLINICAL PHARMACOLOGY

12.1 Mechanism of Action

Eptinezumab-jjmr is a humanized monoclonal antibody that binds to calcitonin gene-related peptide (CGRP) ligand and blocks its binding to the receptor.

12.2 Pharmacodynamics

The relationship between the pharmacodynamic activity and the mechanism(s) by which eptinezumab-jjmr exerts its clinical effects is unknown.

12.3 Pharmacokinetics

Eptinezumab-jjmr exhibits linear pharmacokinetics and exposure increases proportionally with doses from 100 mg to 300 mg after intravenous administration. Steady-state plasma concentration is attained after the first dose with a once every 3-month dosing schedule.

Distribution

The central volume of distribution (Vc) for eptinezumab-jjmr is approximately 3.7 liters.

Metabolism & Elimination

Eptinezumab-jjmr is expected to be degraded by proteolytic enzymes into small peptides and amino acids.

The apparent clearance of eptinezumab-jjmr was 0.006 L/h, and the terminal elimination half-life was approximately 27 days.

Specific Populations

A population pharmacokinetic analysis assessing the effects of age, race, sex, and body weight did not suggest any clinically significant impact of these covariates on eptinezumab exposures.

Patients with Renal or Hepatic Impairment

No dedicated studies were conducted to assess the effects of renal or hepatic impairment on the pharmacokinetics of eptinezumab-jjmr. However, hepatic or renal impairment is not expected to affect the pharmacokinetics of eptinezumab-jjmr. A population pharmacokinetic analysis of integrated data from eptinezumab-jjmr clinical studies did not reveal clinically significant impact on pharmacokinetics of patients with hepatic or renal impairment.

Drug Interaction Studies

P450 Enzymes

Eptinezumab-jjmr is not metabolized by cytochrome P450 enzymes; therefore, interactions with concomitant medications that are substrates, inducers, or inhibitors of cytochrome P450 enzymes are unlikely.

Sumatriptan

The co-administration of a single dose of 300 mg eptinezumab-jjmr administered as an intravenous infusion (over a period of 1 hour ± 15 min) with a single dose of 6 mg sumatriptan administered subcutaneously did not significantly influence the pharmacokinetics of eptinezumab-jjmr or sumatriptan.

12.6 Immunogenicity

The observed incidence of anti-drug antibodies is highly dependent on the sensitivity and speciﬁcity of the assay. Differences in assay methods preclude meaningful comparisons of the incidence of anti-drug antibodies in the studies described below with the incidence of anti-drug antibodies in other studies, including those of eptinezumab-jjmr.

In patients receiving VYEPTI 100 mg or 300 mg every 3 months, the incidence of anti-eptinezumab-jjmr antibody development in Study 1 (up to 56 weeks) was 20.6% (92/447), and 41.3% (38/92) of those patients developed anti-eptinezumab-jjmr neutralizing antibodies. In Study 2 (up to 32 weeks), the incidence of anti-eptinezumab-jjmr antibody development was 18.3% (129/706), and 34.9% (45/129) of those patients developed anti-eptinezumab-jjmr neutralizing antibodies. In an open-label study with 84 weeks of treatment, 18% (23/128) of patients developed anti-eptinezumab-jjmr antibodies, and 39% (9/23) of those patients developed anti-eptinezumab-jjmr neutralizing antibodies.

Although the results from both studies showed no clear evidence of an impact from development of anti-eptinezumab-jjmr antibodies, including neutralizing antibodies, on the safety and efficacy profiles of VYEPTI, the available data are too limited to make definitive conclusions.

13 NONCLINICAL TOXICOLOGY

13.1 Carcinogenesis, Mutagenesis, Impairment of Fertility

Carcinogenesis

The carcinogenic potential of eptinezumab-jjmr has not been assessed.

Mutagenesis

Genetic toxicology studies of eptinezumab-jjmr have not been conducted.

Impairment of Fertility

When eptinezumab-jjmr (0, 75, or 150 mg/kg) was administered weekly by intravenous injection to male and female rats prior to and during mating and continuing in females to gestation day 3-4, no adverse effects on fertility were observed. The higher dose tested (150 mg/kg) is 30 times the maximum recommended human dose of 300 mg, on a body weight basis (mg/kg).

14 CLINICAL STUDIES

The efficacy of VYEPTI was evaluated in three randomized, multicenter, placebo-controlled double-blind studies that enrolled patients with episodic and chronic migraine who were eligible for preventive treatment of migraine. In Study 1, which included patients with episodic migraine, and Study 2, which included patients with chronic migraine, either 100 mg or 300 mg VYEPTI was administered by intravenous infusion every 3 months. In Study 3, 100 mg VYEPTI was administered as a single intravenous infusion to patients with episodic or chronic migraine who were eligible for preventive migraine treatment and who had a concurrent migraine.

Study 1: Episodic Migraine

Study 1 (NCT02559895) included adults with a history of episodic migraine (4 to 14 headache days per month, of which at least 4 were migraine days). A total of 665 patients were randomized to receive placebo (N=222), 100 mg VYEPTI (N=221), or 300 mg VYEPTI (N=222) every 3 months for 12 months. Patients were allowed to use concurrent acute migraine or headache medications, including migraine-specific medications (i.e., triptans, ergotamine derivatives), during the trial.

The study excluded patients with a history of cardiovascular disease (hypertension, ischemic heart disease), neurological disease, or cerebrovascular disease.

The primary efficacy endpoint was the change from baseline in mean monthly migraine days over Months 1-3. Secondary endpoints included the percentages of patients with 50% or greater, and 75% or greater reductions from baseline in monthly migraine days over Months 1-3.

Patients had a median age of 39 years (range: 18 to 71 years), 84% were female, and 84% were white. The mean migraine frequency at baseline was approximately 8.6 migraine days per month and was similar across treatment groups.

VYEPTI treatment demonstrated statistically significant improvements compared to placebo for the primary efficacy endpoint, as shown in Table 2; secondary endpoints are also summarized in Table 2.

Table 2. Efficacy Endpoint Results in Study 1

 | VYEPTI 100 mg N=221 | VYEPTI 300 mg N=222 | Placebo N=222
Monthly Migraine Days (MMD) – Months 1-3
Change from baseline | -3.9 | -4.3 | -3.2
Difference from placebo | -0.7 | -1.1
p-value | 0.018 | <0.001
≥50% MMD responders – Months 1-3
% Responders | 49.8% | 56.3% | 37.4%
Difference from placebo | 12.4% | 18.9%
p-value | 0.009* | <0.001
≥75% MMD responders – Months 1-3
% Responders | 22.2% | 29.7% | 16.2%
Difference from placebo | 6.0% | 13.5%
p-value | NS** | <0.001

* Nominal statistical significance

** NS = Not statistically significant

Figure 1 shows the mean change from baseline in average monthly migraine days in Study 1. Patients treated with VYEPTI at both doses had greater mean decreases from baseline in mean monthly migraine days over Months 1-3 compared to placebo-treated patients.

Figure 1. Change from Baseline in Monthly Migraine Days in Study 1

Figure 2 shows the distribution of change from baseline in mean monthly migraine days through Month 3 by treatment group in 2-day increments.

Figure 2. Distribution of Change from Baseline in Mean Monthly Migraine Days over Months 1 to 3 by Treatment Group in Study 1

Figure 3 demonstrates that greater percentages of placebo-treated patients had migraines on most days during the first 7 days of treatment compared to VYEPTI-treated patients in Study 1.

Figure 3. Percentage of Patients with a Migraine from Day -1 (Day Prior to Infusion) to Day 7 in Study 1

Study 2: Chronic Migraine

Study 2 (NCT02974153) included adults with a history of chronic migraine (15 to 26 headache days per month, of which at least 8 were migraine days). A total of 1072 patients were randomized and received placebo (N=366), 100 mg VYEPTI (N=356), or 300 mg VYEPTI (N=350) every 3 months for 6 months. Patients were allowed to use and to continue an established stable regimen of acute migraine or headache preventive medication (except onabotulinumtoxinA). Patients with a dual diagnosis of chronic migraine and medication overuse headache attributable to acute medication overuse (triptans, ergotamine, or combination analgesics greater than 10 days per month) were included in the study population. Patients using opioids or butalbital-containing products greater than 4 days per month were not allowed.

The study excluded patients with a history of cardiovascular disease (hypertension, ischemic heart disease), neurological disease, or cerebrovascular disease.

The primary efficacy endpoint was the change from baseline in mean monthly migraine days over Months 1-3. Secondary endpoints included the percentages of patients with 50% or greater and 75% or greater reductions from baseline in monthly migraine days over Months 1-3.

Patients had a median age of 41 years (range: 18 to 65 years), 88% were female, and 91% were white. Forty-one percent of patients were taking concomitant preventive medication for migraine. The mean migraine frequency at baseline was approximately 16.1 migraine days per month and was similar across treatment groups.

VYEPTI treatment demonstrated statistically significant improvements compared to placebo for the primary efficacy endpoint, as shown in Table 3; secondary endpoints are also summarized in Table 3.

Table 3. Efficacy Endpoint Results in Study 2

 | VYEPTI100 mg N=356 | VYEPTI300 mg N=350 | Placebo N=366
Monthly Migraine Days (MMD) – Months 1-3
Change from baseline | -7.7 | -8.2 | -5.6
Difference from placebo | -2.0 | -2.6
p-value | <0.001 | <0.001
≥50% MMD responders –Months 1-3
% Responders | 57.6% | 61.4% | 39.3%
Difference from placebo | 18.2% | 22.1%
p-value | <0.001 | <0.001
≥75% MMD responders –Months 1-3
% Responders | 26.7% | 33.1% | 15.0%
Difference from placebo | 11.7% | 18.1%
p-value | <0.001 | <0.001

Figure 4 shows the mean change from baseline in average monthly migraine days for Study 2. Patients treated with VYEPTI at both doses had greater mean decreases from baseline in mean monthly migraine days over Month 1-3 compared to placebo-treated patients.

Figure 4. Change from Baseline in Monthly Migraine Days in Study 2

Figure 5 shows the distribution of change from baseline in mean monthly migraine days through Month 3 by treatment group in 3-day increments.

Figure 5. Distribution of Change from Baseline in Mean Monthly Migraine Days over Months 1-3 by Treatment Group in Study 2

Figure 6 demonstrates that greater percentages of placebo-treated patients had migraines on individual days during the first 7 days of treatment compared to VYEPTI-treated patients in Study 2.

Figure 6. Percentage of Patients with a Migraine from Day -1 (Day Prior to Infusion) to Day 7 in Study 2

Study 3: Episodic Migraine or Chronic Migraine

Study 3 (NCT01719055) included adults who were candidates for preventive migraine therapy with VYEPTI and presented with a concurrent moderate to severe migraine on the day of infusion. A total of 480 patients were randomized to receive 100 mg VYEPTI (n=238) or placebo (n=242) as a single dose. VYEPTI demonstrated statistically significant improvements in headache pain freedom at 2 hours (VYEPTI 23.5% vs placebo 12%; p<0.001) and absence of most bothersome symptom (such as nausea, photophobia, or phonophobia) at 2 hours (VYEPTI 55.5% vs placebo 35.8%; p< 0.001) as compared to placebo. The dose of 300 mg VYEPTI was not evaluated in Study 3.

16 HOW SUPPLIED/STORAGE AND HANDLING

16.1 How Supplied

VYEPTI (eptinezumab-jjmr) injection is a clear to slightly opalescent, colorless to brownish-yellow solution supplied as:

Carton containing one 100 mg/mL single-dose vial - NDC 67386-130-51.

16.2 Storage and Handling

Store refrigerated at 2°C to 8°C (36°F to 46°F) in the original carton to protect from light until time of use. Do not freeze or shake.

The vial stopper is not made with natural rubber latex.

17 PATIENT COUNSELING INFORMATION

Advise the patient to read the FDA-approved patient labeling (Patient Information).

Hypersensitivity Reactions

Inform patients about the signs and symptoms of hypersensitivity reactions and that these reactions can occur with VYEPTI. Advise patients to contact their healthcare provider immediately if signs or symptoms of hypersensitivity reactions occur [see Warnings and Precautions (5.1)].

Hypertension

Inform patients that hypertension can develop or pre-existing hypertension can worsen with VYEPTI, and that they should contact their healthcare provider if they experience elevation in their blood pressure [see Warnings and Precautions (5.2)].

Raynaud’s Phenomenon

Inform patients that Raynaud’s phenomenon can develop or worsen with VYEPTI. Advise patients to discontinue VYEPTI treatment and contact their healthcare provider if they experience signs or symptoms of Raynaud’s phenomenon [see Warnings and Precautions (5.3)].

Pregnancy Exposure Registry

Advise patients that there is a pregnancy exposure registry that monitors pregnancy outcomes in women exposed to VYEPTI during pregnancy [see Use in Specific Populations (8.1)].

Lactation

Inform patients to notify their healthcare provider if they are breastfeeding or plan to breastfeed [see Use in Specific Populations (8.2)].

Manufactured by:

Lundbeck Seattle BioPharmaceuticals, Inc.

11804 North Creek Parkway South

Bothell, WA 98011 USA

U.S. License No. 2097

Vyepti is a registered trademark of Lundbeck Seattle BioPharmaceuticals, Inc.

PATIENT PACKAGE INSERT

PATIENT INFORMATION

VYEPTI®(vye ep' tee)

(eptinezumab-jjmr)

injection, for intravenous use

What is VYEPTI?

VYEPTI is a prescription medicine used for the preventive treatment of migraine in adults.

It is not known if VYEPTI is safe and effective in children.

Do not receive VYEPTI if you are allergic to eptinezumab-jjmr or any of the ingredients in VYEPTI. See the end of this Patient Information leaflet for a complete list of ingredients in VYEPTI.

Before you receive VYEPTI, tell your healthcare provider about all of your medical conditions, including if you:

- have high blood pressure.
- have circulation problems in your fingers and toes.
- are pregnant or plan to become pregnant. It is not known if VYEPTI will harm your unborn baby.
  - Pregnancy Registry: There is a pregnancy registry for women who take VYEPTI. The purpose of this registry is to collect information about the health of you and your baby. You may enroll yourself by calling 1-855-810-8549 or by visiting www.vyeptipregnancyregistry.lundbeck.com. Or you may talk to your healthcare provider about how you can take part in this registry.

- are breastfeeding or plan to breastfeed. It is not known if VYEPTI passes into your breast milk. Talk to your healthcare provider about the best way to feed your baby while using VYEPTI.

Tell your healthcare provider about all the medicines you take, including prescription and over-the-counter medicines, vitamins, and herbal supplements.

How will I receive VYEPTI?

- VYEPTI will be given by a healthcare provider in a healthcare setting.
- VYEPTI is given by intravenous (IV) infusion in your vein.
- VYEPTI will be given over 30 minutes every 3 months.

If you have questions about your infusion schedule, ask your healthcare provider.

What are the possible side effects of VYEPTI?

VYEPTI may cause serious side effects, including:

- Allergic reactions. Allergic reactions can happen after receiving VYEPTI. Call your healthcare provider or get emergency medical help right away if you have any of the following symptoms of an allergic reaction:
  o rash
  o swelling of your face, lips, tongue or throat
  o trouble breathing
  o hives
  o redness in your face

- High blood pressure. High blood pressure or worsening of high blood pressure can happen after receiving VYEPTI. Contact your healthcare provider if you have an increase in blood pressure.
- Raynaud’s phenomenon. A type of circulation problem can worsen or happen after receiving VYEPTI. Raynaud’s phenomenon can lead to your fingers or toes feeling numb, cool, or painful, or changing color from pale, to blue, to red. Contact your healthcare provider if these symptoms occur.

The most common side effects of VYEPTI include:

- stuffy nose and scratchy throat
- allergic reactions

These are not all of the possible side effects of VYEPTI.

Call your doctor for medical advice about side effects. You may report side effects to FDA at 1-800-FDA-1088.

General information about the safe and effective use of VYEPTI.

Medicines are sometimes prescribed for purposes other than those listed in the Patient Information leaflet.

You can ask your pharmacist or healthcare provider for information about VYEPTI that is written for health professionals.

What are the ingredients in VYEPTI?

Active ingredient: eptinezumab-jjmr

Inactive ingredients: L-histidine, L-histidine hydrochloride monohydrate, polysorbate 80, sorbitol, and Water for Injection.

The vial stopper is not made with natural rubber latex.

Manufactured by: Lundbeck Seattle BioPharmaceuticals, Inc., 11804 North Creek Parkway South, Bothell, WA 98011

US License Number: 2097

Vyepti is a registered trademark of Lundbeck Seattle BioPharmaceuticals, Inc.

For more information, call 1-833-4-VYEPTI (833-489-3784) or go to www.Vyepti.com

This Patient Information has been approved by the U.S. Food and Drug Administration. Revised: 10/2025

PRINCIPAL DISPLAY PANEL

NDC 67386-130-51

VYEPTITM (vye ep' tee)

(eptinezumab-jjmr)

injection, for intravenous use

100 mg/mL

PRINCIPAL DISPLAY PANEL

NDC 67386-130-91
VYEPTITM (vye ep' tee)
(eptinezumab-jjmr)
injection, for intravenous use
100 mg/mL
Professional Sample

Professional Sample